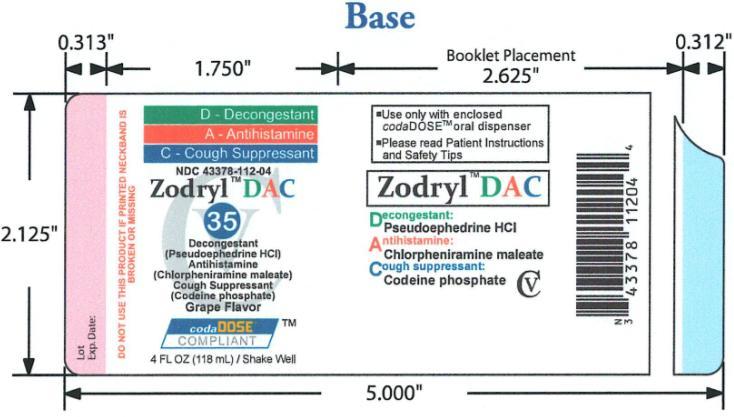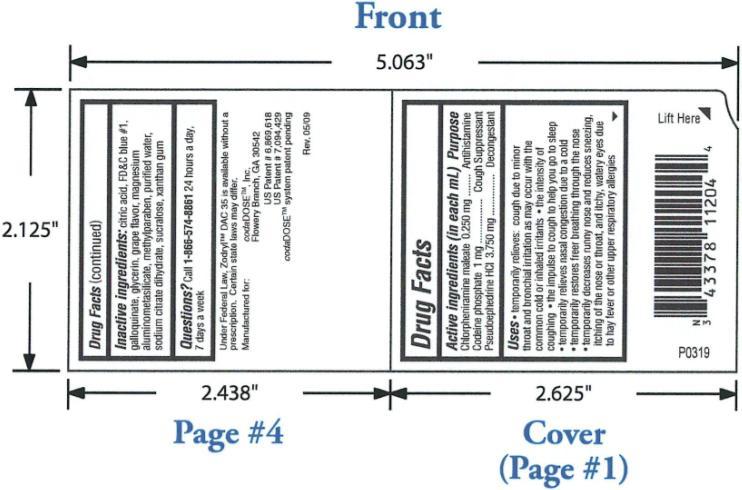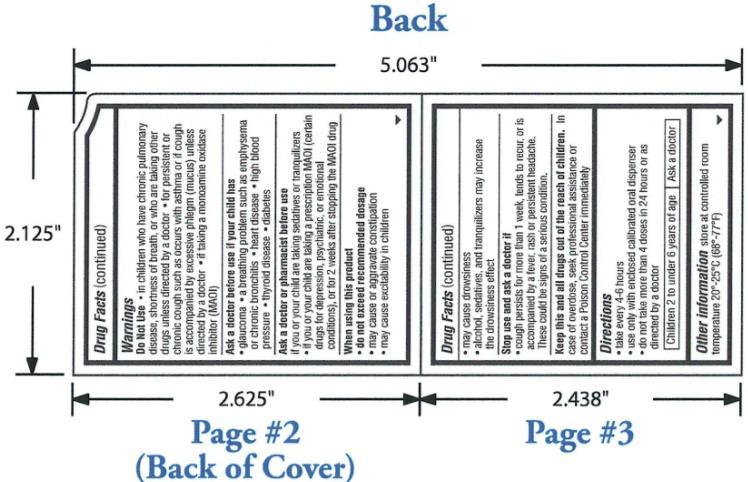 DRUG LABEL: Zodryl DAC 35
NDC: 43378-112 | Form: SUSPENSION
Manufacturer: CodaDose Inc.
Category: otc | Type: HUMAN OTC DRUG LABEL
Date: 20090922
DEA Schedule: CV

ACTIVE INGREDIENTS: CHLORPHENIRAMINE MALEATE 1 mg/4 mL; CODEINE PHOSPHATE 4 mg/4 mL; PSEUDOEPHEDRINE HYDROCHLORIDE 15 mg/4 mL
INACTIVE INGREDIENTS: ANHYDROUS CITRIC ACID; FD&C BLUE NO. 1; TANNIC ACID; GLYCERIN; MAGNESIUM ALUMINUM SILICATE; METHYLPARABEN; WATER; SODIUM CITRATE; SUCRALOSE; XANTHAN GUM

ZODRYL DAC 35 – chlorpheniramine maleate, codeine phosphate, and pseudoephedrine hydrochloride suspension

OTC - ACTIVE INGREDIENT

Chlorpheniramine Maleate 0.250 mg/1mL: antihistamine; Codeine Phosphate 1 mg/1mL: cough suppressant; Pseudoephedrine Hydrochloride 3.750 mg/1mL: decongestant

PURPOSE

Temporarily relieves: cough due to minor throat and bronchial irritation as may occur with the common cold or inhaled irritants; the intensity of coughing; the impulse to cough to help you go to sleep; temporarily relieves nasal congestion due to a cold; temporarily restores freer breathing through the nose; temporarily decreases runny nose and reduces sneezing, itching of the nose or throat, and itchy, watery eyes due to hay fever or other upper respiratory allergies

Warnings

OTC - DO NOT USE

in children who have chronic pulmonary disease, shortness of breath, or who are taking other drugs unless directed by a doctor; for persistent or chronic cough such as occurs with asthma or if cough is accompanied by excessive phlegm (mucus) unless directed by a doctor; if taking a monoamine oxidase inhibitor (MAOI)

OTC - ASK DOCTOR

if your child has glaucoma, a breathing problem such as emphysema or chronic bronchitis, heart disease, high blood pressure, thyroid disease, diabetes.

OTC - ASK DOCTOR/PHARMACIST SECTION

if you or your child are taking sedatives or tranquilizers; if you or your child are taking prescription MAOI (certain drugs for depression, psychiatric, or emotional conditions), or for 2 weeks after stopping the MAOI drug.

OTC - WHEN USING THIS PRODUCT

do not exceed recommended dosage; may cause or aggravate constipation; may cause excitability in children; may cause drowsiness; alcohol, sedatives, and tranquilizers may increase the drowsiness effect

OTC - STOP USE AND ASK A DOCTOR IF

cough persists for more than 1 week, tends to recur, or is accompanied by a fever, rash, or persistent headache. These could be signs of a serious condition.

OTC - KEEP THESE AND ALL DRUGS OUT OF REACH OF CHILDREN

In case of overdose, seek professional assistance for contact a Poison Control Center immediately.

Directions:

- Take every 4-6 hours
- Use only with enclosed calibrated oral dispenser
- Do not take more than 4 doses in 24 hours or as directed by a doctor

Children 2 to under 6 years of age: ask a doctor

Other information store at controlled room temperature 20°-25°C (68°-77°F).

INACTIVE INGREDIENT

citric acid, FD&C blue#1, galloquinate, glycerin, grape flavor, magnesium aluminometasilicate, methylparaben, purified water, sodium citrate dihydrate, sucralose, xanthan gum

OTC – QUESTIONS SECTION

Call 1-866-574-8861 24 hours a day, 7 days a week.

PACKAGE LABEL.PRINCIPAL DISPLAY PANEL

Figure 1. Primary Label- Front Page
Figure 2. Primary Label – Second Page
Figure 3. Primary Label – Last Page